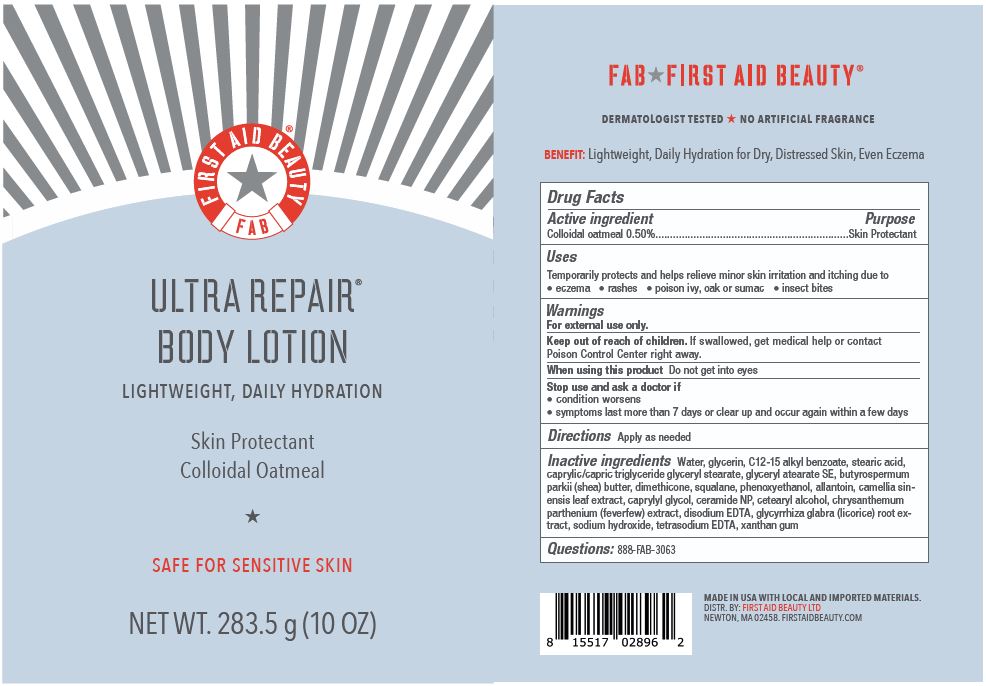 DRUG LABEL: First Aid Beauty FAB Ultra Repair Body Skin Protectant
NDC: 69423-726 | Form: LOTION
Manufacturer: The Procter & Gamble Manufacturing Company
Category: otc | Type: HUMAN OTC DRUG LABEL
Date: 20251218

ACTIVE INGREDIENTS: OATMEAL 0.5 g/100 g
INACTIVE INGREDIENTS: CETOSTEARYL ALCOHOL; SQUALANE; DIMETHICONE; EDETATE DISODIUM; GLYCERYL STEARATE SE; ALKYL (C12-15) BENZOATE; GREEN TEA LEAF; CAPRYLYL GLYCOL; SODIUM HYDROXIDE; PHENOXYETHANOL; SHEA BUTTER; GLYCYRRHIZA GLABRA; WATER; GLYCERIN; ALLANTOIN; GLYCERYL MONOSTEARATE; MEDIUM-CHAIN TRIGLYCERIDES; STEARIC ACID; XANTHAN GUM; CERAMIDE NP; TANACETUM PARTHENIUM; EDETATE SODIUM

First Aid Beauty FAB Ultra Repair Body Lotion

Drug Facts

Active ingredients

Colloidal Oatmeal 0.5%

Purpose

Skin Protectant

Uses

- Temporarily protects and helps relieve minor skin irritation and itching due to eczema, rashes, poison ivy, oak or sumac, insect bites

Warnings

For external use only.

Keep out of reach of children. If swallowed, get medical help or contact a Poison Control Center right away.

WHEN USING

Do not get into eyes.

Stop use and ask a doctor if condition worsens, symptoms last more than 7 days or clear up and occur again within a few days

Directions

Apply as needed

INACTIVE INGREDIENT

Water, glycerin, C12-15 alkyl benzoate, stearic acid, caprylic/capric triglyceride glyceryl stearate, glyceryl atearate SE, butyrospermum parkii (shea) butter, dimethicone, squalane, phenoxyethanol, allantoin, camellia sinensis leaf extract, caprylyl glycol, ceramide NP, cetearyl alcohol, chrysanthemum parthenium (feverfew) extract, disodium EDTA, glycyrrhiza glabra (licorice) root extract, sodium hydroxide, tetrasodium EDTA, xanthan gum

Questions:

888-FAB-3063

MADE IN USA

FIRST AID BEAUTY LTD

NEWTON, MA 02458

WWW.FIRSTAIDBEAUTY.COM

PRINCIPAL DISPLAY PANEL - 283.5 g (10 oz)

First Aid Beauty

FAB

Ultra Repair Body Lotion

Lightweight, Daily Hydration

Skin Protectant Colloidal Oatmeal

Net Wt. 283.5 g (10 oz)